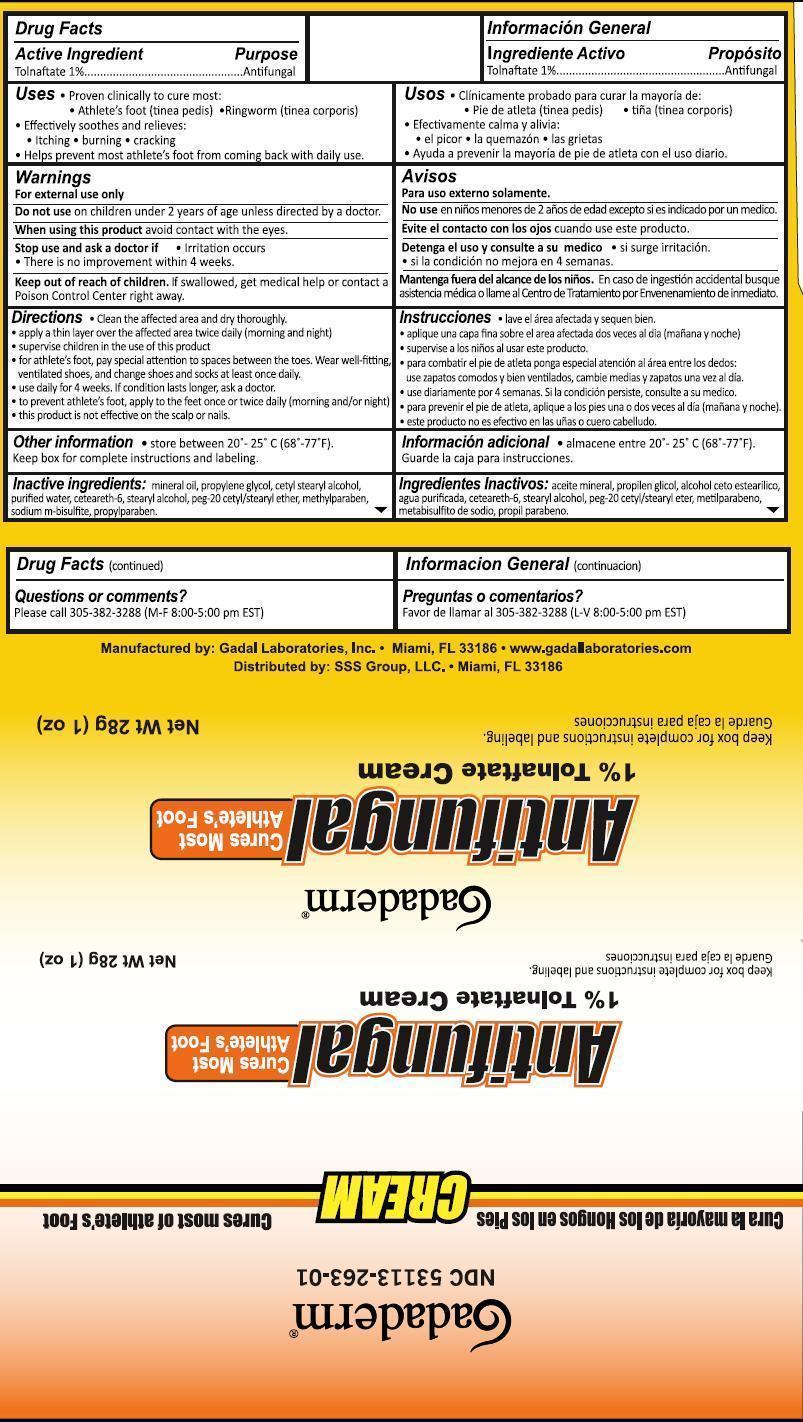 DRUG LABEL: Gadaderm Antifungal
NDC: 53113-263 | Form: CREAM
Manufacturer: Gadal Laboratories Inc
Category: otc | Type: HUMAN OTC DRUG LABEL
Date: 20130927

ACTIVE INGREDIENTS: TOLNAFTATE 1 g/100 g
INACTIVE INGREDIENTS: MINERAL OIL; PROPYLENE GLYCOL; CETOSTEARYL ALCOHOL; WATER; CETEARETH-6; STEARYL ALCOHOL; POLYOXYL 20 CETOSTEARYL ETHER; METHYLPARABEN; PROPYLPARABEN; SODIUM BISULFITE

Active Ingredient Purpose

Tolnaftate 1% Antifungal

Purpose

Antifungal

Uses

- Proven clinically to cure most:
- Athlete's foot (tinea pedis)
- Ringworm (tinea corporis)
- Effectively soothes and relieves:
- itching
- burning
- cracking
- Helps prevent most athlete's foot from coming back with daily use.

Warnings: For External Use Only.

Do not use on children under 2 years of age unless directed by a doctor.

When using this product avoid contact with the eyes.

Stop use and ask a doctor if

- irritation occurs
- There is no improvement within 4 weeks.

Keep out of reach of children. If swallowed, get medical help or contact a Poison Control Center right away

Directions

- Clean the affected area and dry thoroughly.
- apply a thin layer over the affected area twice daily (morning and night)
- supervise children in the use of this product
- for athlete's foot, pay special attention to spaces between the toes. Wear well-fitting, ventilated shoes, and change shoes and socks at least once daily.
- use daily for 4 weeks. If condition lasts longer, ask a doctor.
- to prevent athlete's foot, apply to the feet once or twice daily (morning and/or night)
- this product is not effective on the scalp or nails

INACTIVE INGREDIENT

Inactive ingredients Mineral oil, propylene glycol, cety stearyl alcohol, purified water, ceteareth-6, stearyl alcohol, PEG-20 cetyl/stearyl ether, methylparaben, sodium m-bisulfite, propylparaben

QUESTIONS

SSS Group LLC.

Miami, Fl 33186